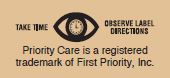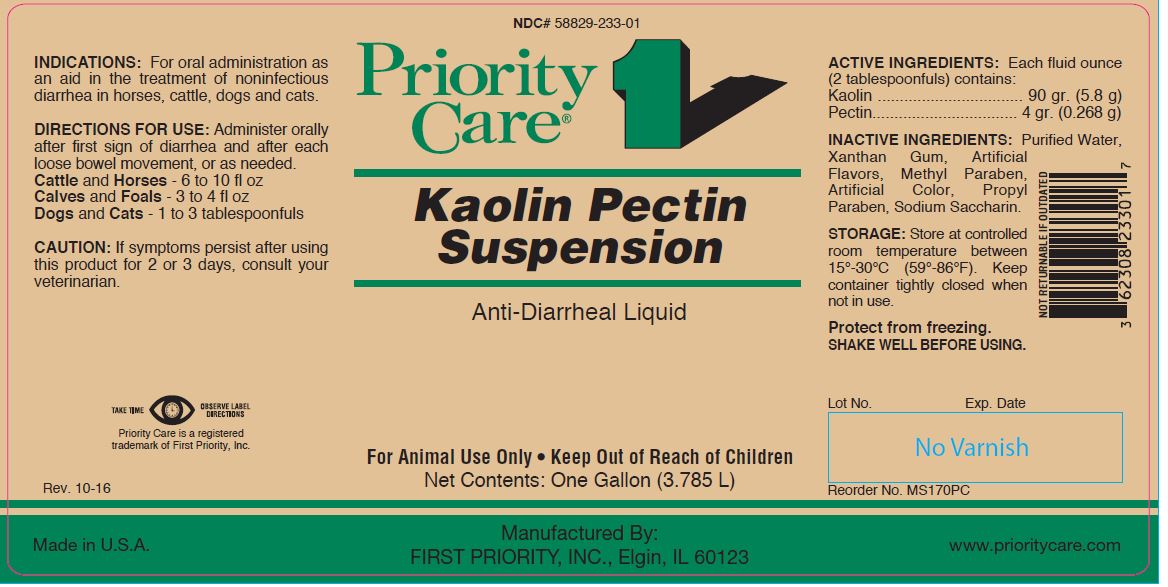 DRUG LABEL: Kaolin Pectin
NDC: 58829-233 | Form: SUSPENSION
Manufacturer: FIRST PRIORITY INCORPORATED
Category: animal | Type: OTC ANIMAL DRUG LABEL
Date: 20170926

ACTIVE INGREDIENTS: KAOLIN 208.1 g/1 L; PECTIN, CITRUS 8.8 g/1 L

Kaolin Pectin Suspension

PURPOSE

Anti-Diarrheal Liquid

KEEP OUT OF REACH OF CHILDREN

For Animal Use Only • Keep Out of Reach of Children

INDICATIONS:

For oral administration as an aid in the treatment of noninfectious diarrhea in horses, cattle, dogs and cats.

DIRECTIONS FOR USE:

Administer orally after first sign of diarrhea and after each loose bowel movement, or as needed.
Cattle and Horses - 6 to 10 fl oz
Calves and Foals - 3 to 4 fl oz
Dogs and Cats - 1 to 3 tablespoonfuls

CAUTION:

If symptoms persist after using this product for 2 or 3 days, consult your veterinarian.

ACTIVE INGREDIENTS:

Each fluid ounce (2 tablespoonfuls) contains:
Kaolin ................................. 90 gr. (5.8 g)
Pectin................................. 4 gr. (0.268 g)

INACTIVE INGREDIENTS:

Purified Water, Xanthan Gum, Artificial Flavors, Methyl Paraben, Artificial Color, Propyl Paraben, Sodium Saccharin.

STORAGE:

Store at controlled room temperature between 15º to 30ºC (59º-86ºF). Keep container tightly closed when not in use.

Protect from freezing.
SHAKE WELL BEFORE USING.

Net Contents:

One Gallon (3.785 L) Reorder No. MS170PC

INFORMATION FOR OWNERS/CAREGIVERS

Made in U.S.A.

Manufactured By:
FIRST PRIORITY, INC., Elgin, IL 60123

www.prioritycare.com